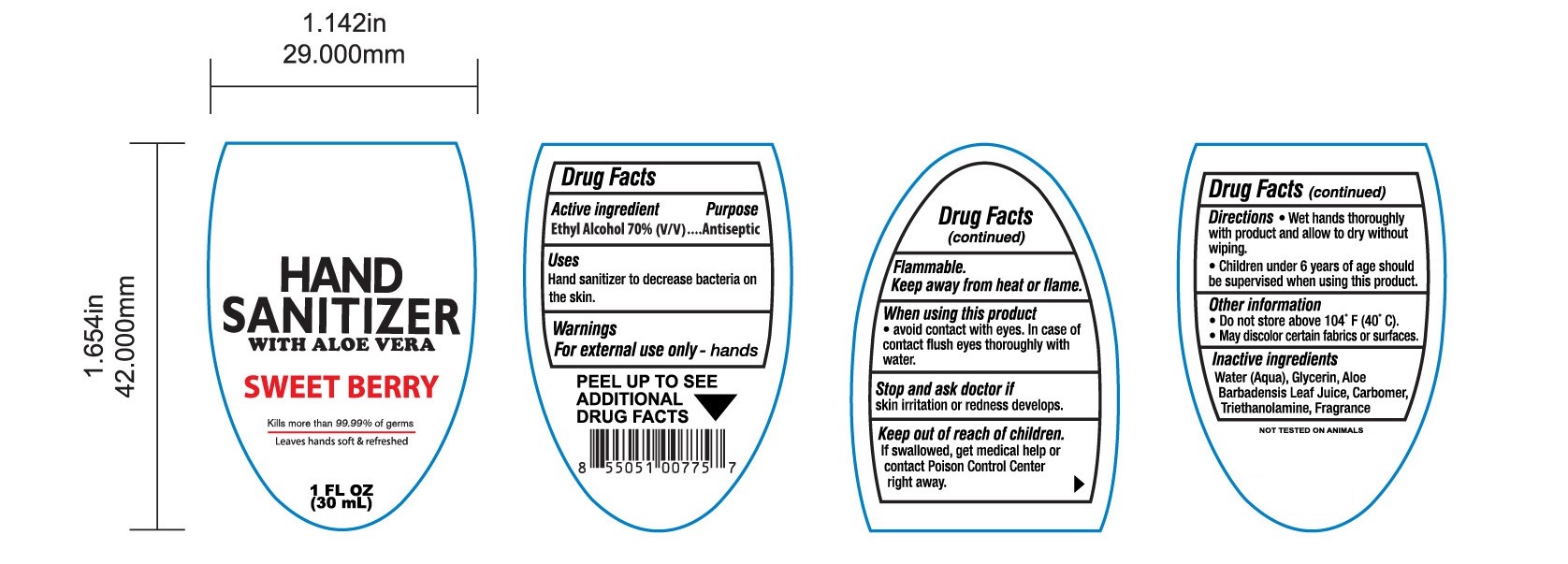 DRUG LABEL: HAND SANITIZER
NDC: 47993-290 | Form: GEL
Manufacturer: NINGBO JIANGBEI OCEAN STAR TRADING CO.,LTD
Category: otc | Type: HUMAN OTC DRUG LABEL
Date: 20201105

ACTIVE INGREDIENTS: ALCOHOL 70 mL/100 mL
INACTIVE INGREDIENTS: WATER; GLYCERIN; ALOE VERA LEAF; CARBOMER 940; TRIETHANOLAMINE BENZOATE

47993-290

Active ingredients

Ethyl Alcohol 70%(V/V)

PURPOSE

Antiseptic

Uses：

Hand sanitizer to decrease bacteria on the skin.

Warnings：

For external use only-hands

Flammable.

Keep away from heat or flame.

When using this product

- avoid contact with eyes. In case of contact flush eyes thoroughly with water.

Stop and ask doctor if

skin irritation or redness develops.

Keep out of reach of children.

If swallowed, get medical help or contact Poison Control Center right away.

Directions:

- Wet hands thoroughly with product and allow to dry without wiping.
- Children under 6 years of age should be supervised when using this product.

Other information:

- Do not store above 104℉ (40℃).
- May discolor certain fabrics or surfaces.

Inactive Ingredients:

Water (Aqua),Glycerin,Aloe Barbadensis Leaf Juice,Carbomer,Triethanolamine,Fragrance